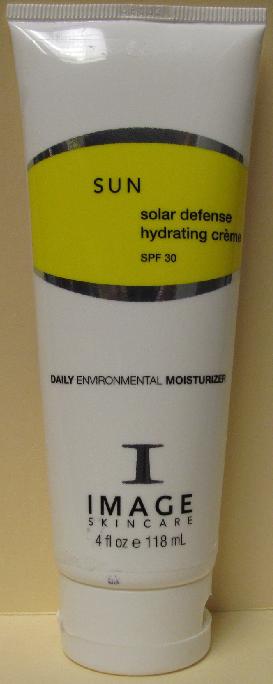 DRUG LABEL: SUN Solar Defense Hydrating 
NDC: 62742-4037 | Form: CREAM
Manufacturer: Allure Labs, Inc.
Category: otc | Type: HUMAN OTC DRUG LABEL
Date: 20100630

ACTIVE INGREDIENTS: ZINC OXIDE 50 mg/1 mL; OCTINOXATE 75 mg/1 mL; OXYBENZONE 30 mg/1 mL; OCTISALATE 50 mg/1 mL

Drug Facts

Active Ingredients:

Zinc Oxide 5%

Ethylhexyl Methoxycinnamate (Octinoxate) 7.5%

Benzophenone-3 3%

Ethylhexyl Salicylate (Octisalate) 5%

Uses:

A hydrating UVA/UVB broad spectrum daily moisturizer. Provides ultimate protection against the aging effects of the sun and other environmental exposures. Enriched with essential vitamins and anti-oxidants that prevent free radical damage and preserving skin hydration for the entire day.

Water-resistant

Paraben-free

Directions:

Apply to cleaned skin every morning for ultimate protection.

Indications: Dry, dehydrated, rosacea, sensitive.

Warnings:

For External use only

When using this product-

Keep out of eyes. If contact occurs rinse with water.

Discontinue use if irritation or redness occurs

Keep out of reach of children

Inactive Ingredients:

Deionized water (Aqua), C12-15 Alkyl Benzoate, Glyceryl Stearate (and) PEG-100 Stearate, Glycerin, Sodium Hyaluronate, Imperata Cylindrica Root Extract, Octyl Dodecyl Neopentanoate, Sorbitol, Caprylic/Capric Truglyceride, Camellia sinensis (Green Tea) Leaf Extract, Biosaccharide Gum-1, Algae Extract and Mugwort Extract, Caprylyl Glycol and Phnoxyethanol and Hexylene Glycol, Sodium PCA, Lecithin, Sorbitan Stearate, Symphytum Officinale Extract and Plantago Ovata Seed Extract, Yeast Extract, Aloe Barbadensis Leaf Extract, Spiraea Ulmaria Flower Extract (and) Centella Asiatica Extract, Magnesium Aluminum Silicate, Tocopheryl Acetate, Ascorbyl Palmitate, Disodium EDTA, Dipotassium Glycyrrizate, Amino Acids.

PACKAGE LABEL

Image of the Product:

Distributor:

Image International

Palm Beach, FL 33411 USA

www.imageskincare.com